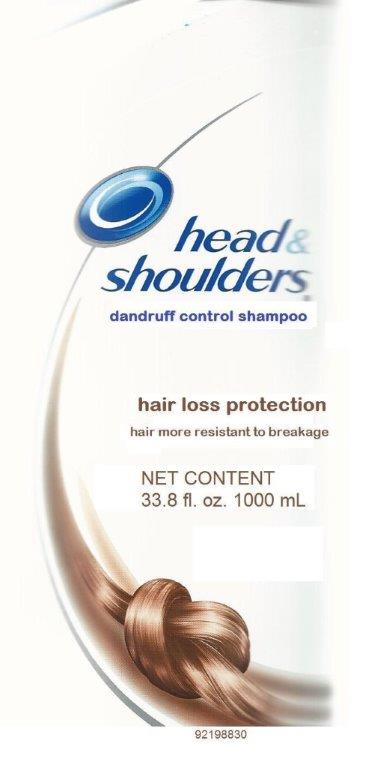 DRUG LABEL: HEAD AND SHOULDERS
NDC: 69772-141 | Form: LOTION/SHAMPOO
Manufacturer: TERESA CECENA DBA GENESIS
Category: otc | Type: HUMAN OTC DRUG LABEL
Date: 20150512

ACTIVE INGREDIENTS: PYRITHIONE ZINC 0.01 g/1 mL
INACTIVE INGREDIENTS: WATER; SODIUM LAURETH SULFATE; SODIUM LAURYL SULFATE; COCO MONOETHANOLAMIDE; BENZYL ALCOHOL; ALPHA-TOCOPHEROL ACETATE; FD&C YELLOW NO. 5; METHYLCHLOROISOTHIAZOLINONE; METHYLISOTHIAZOLINONE; FD&C BLUE NO. 1; ZINC CARBONATE; GLYCOL DISTEARATE; DIMETHICONE; GUAR HYDROXYPROPYLTRIMONIUM CHLORIDE (1.7 SUBSTITUENTS PER SACCHARIDE); MAGNESIUM SULFATE; SODIUM BENZOATE; MAGNESIUM CARBONATE HYDROXIDE

DRUG FACTS

ACTIVE INGREDIENT

PHYRITHIONE ZINC 1%

PURPOSE

Anti-drandruff

USES

Helps prevent recurrence of flaking and itching associated with drandruff

Help prevent hair loss

WARNINGS

FOR EXTERNAL USE ONLY

WHEN USING THIS PRODUCT

- avoid contact with eyes If contact occurs, rinse eyes thoroughly with water.

STOP USE AND ASK A DOCTOR IF

- condition worsens or does not improve after regular use of this product as directed.\

KEEP THIS AND ALL DRUGS OUT OF REACH OF CHILDREN If swallowed, get medical help or contact a poison control center right away.

DIRECTIONS

- for maximun drandruff control, use every time you shampoo
- wet hair, message onto scalp, rinse, repeat if desired
- For best results use al least twice a week or as directed by a doctor.

INACTIVE INGREDIENT

water, sodium laureth sulfate, sodium lauryl sulfate. Coco monoethanolamide, zinc carbonate, glycol distearate, dimethicone, guar hydroxypropyltrimonium chloride, magnesium sulfate, sodium benzoate, magnesium carbonate hydroxide, benzyl alchohol, tocopheryl acetate, FD&C yellow No5, methylchloroisothiazolinonone, methyllisothiazolinone, FD&C blue No 1

KEEP OUT OF REACH OF CHILDREN

KEEP THIS AND ALL DRUGS OUT OF REACH OF CHILDREN

DIRECTIONS

- FOR MAXIMUN DRANDRUFF CONTROL, USE EVERY TIME YOU SHAMPOO
- WET HAIR, MESSAGE ONTO SCALP, RINSE, REPEAT IF DESIRED
- FOR BEST RESULTS USE AT LEAST TWICE A WEEK OR AS DIRECTED BY A DOCTOR